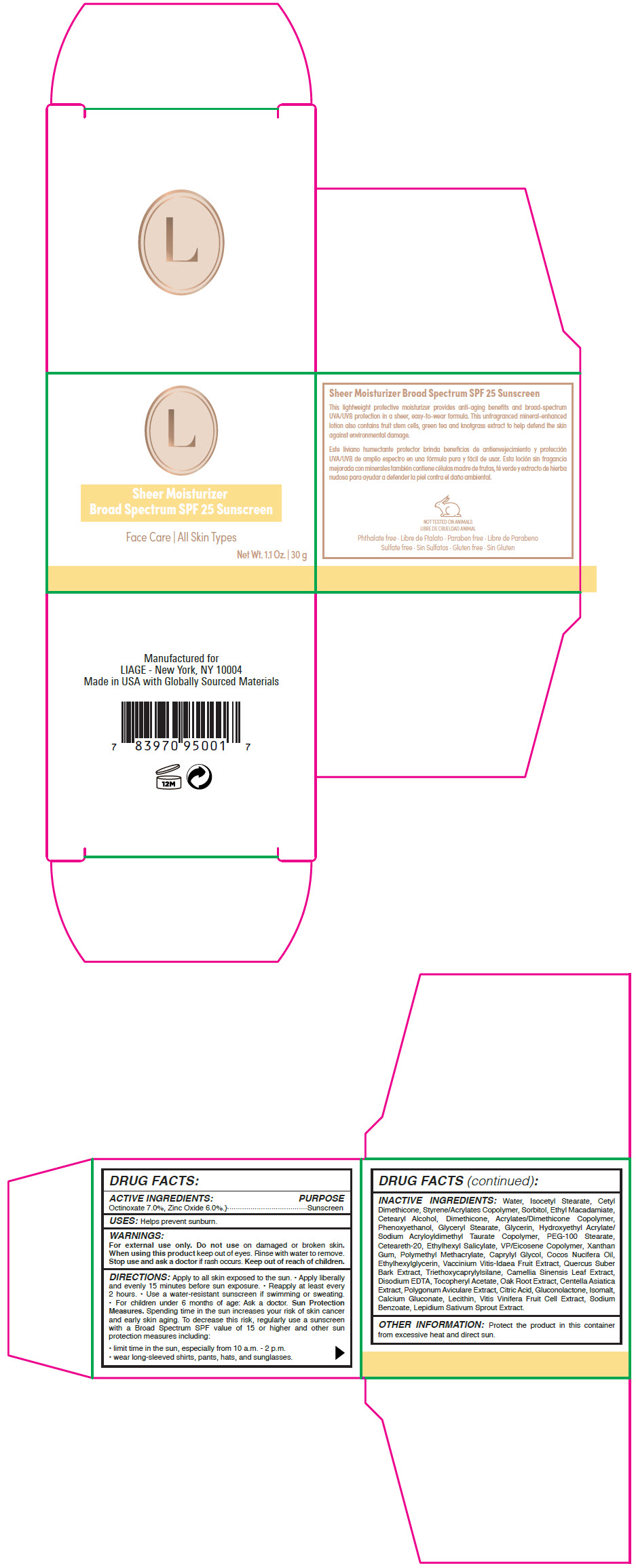 DRUG LABEL: Liage - Sheer Moisturizer Broad Spectrum SPF 25 Sunscreen
NDC: 66163-2604 | Form: LOTION
Manufacturer: Cosmetic Solutions LLC
Category: otc | Type: HUMAN OTC DRUG LABEL
Date: 20220729

ACTIVE INGREDIENTS: Octinoxate 0.07 g/1 g; Zinc Oxide 0.06 g/1 g
INACTIVE INGREDIENTS: Water; Isocetyl Stearate; Sorbitol; Ethyl Macadamiate; Cetostearyl Alcohol; Dimethicone; Phenoxyethanol; Glyceryl Monostearate; Glycerin; Hydroxyethyl Acrylate/Sodium Acryloyldimethyl Taurate Copolymer (100000 MPA.S at 1.5%); PEG-100 Stearate; Polyoxyl 20 Cetostearyl Ether; Octisalate; Xanthan Gum; Poly(Methyl Methacrylate; 450000 MW); Caprylyl Glycol; Ethylhexylglycerin; Lingonberry; Quercus Suber Bark; Triethoxycaprylylsilane; Green Tea Leaf; Edetate Disodium Anhydrous; .Alpha.-Tocopherol Acetate; Centella Asiatica Whole; Polygonum Aviculare Top; Citric Acid Monohydrate; Gluconolactone; Isomalt; Calcium Gluconate; Sodium Benzoate; Garden Cress Sprout

Liage - Sheer Moisturizer Broad Spectrum SPF 25 Sunscreen

DRUG FACTS:

ACTIVE INGREDIENTS

Octinoxate 7.0%, Zinc Oxide 6.0%.

PURPOSE

Sunscreen

USES

Helps prevent sunburn.

WARNINGS

For external use only. Do not use on damaged or broken skin. When using this product keep out of eyes. Rinse with water to remove. Stop use and ask a doctor if rash occurs.

Keep out of reach of children.

DIRECTIONS

Apply to all skin exposed to the sun.

- Apply liberally and evenly 15 minutes before sun exposure.
- Reapply at least every 2 hours.
- Use a water-resistant sunscreen if swimming or sweating.
- For children under 6 months of age: Ask a doctor.

Sun Protection Measures. Spending time in the sun increases your risk of skin cancer and early skin aging. To decrease this risk, regularly use a sunscreen with a Broad Spectrum SPF value of 15 or higher and other sun protection measures including:

- limit time in the sun, especially from 10 a.m. - 2 p.m.
- wear long-sleeved shirts, pants, hats, and sunglasses.

INACTIVE INGREDIENTS

Water, Isocetyl Stearate, Cetyl Dimethicone, Styrene/Acrylates Copolymer, Sorbitol, Ethyl Macadamiate, Cetearyl Alcohol, Dimethicone, Acrylates/Dimethicone Copolymer, Phenoxyethanol, Glyceryl Stearate, Glycerin, Hydroxyethyl Acrylate/ Sodium Acryloyldimethyl Taurate Copolymer, PEG-100 Stearate, Ceteareth-20, Ethylhexyl Salicylate, VP/Eicosene Copolymer, Xanthan Gum, Polymethyl Methacrylate, Caprylyl Glycol, Cocos Nucifera Oil, Ethylhexylglycerin, Vaccinium Vitis-Idaea Fruit Extract, Quercus Suber Bark Extract, Triethoxycaprylylsilane, Camellia Sinensis Leaf Extract, Disodium EDTA, Tocopheryl Acetate, Oak Root Extract, Centella Asiatica Extract, Polygonum Aviculare Extract, Citric Acid, Gluconolactone, Isomalt, Calcium Gluconate, Lecithin, Vitis Vinifera Fruit Cell Extract, Sodium Benzoate, Lepidium Sativum Sprout Extract.

OTHER INFORMATION

Protect the product in this container from excessive heat and direct sun.

PRINCIPAL DISPLAY PANEL - 30 g Jar Carton

Sheer Moisturizer
Broad Spectrum SPF 25 Sunscreen

Face Care | All Skin Types

Net Wt. 1.1 Oz. | 30 g